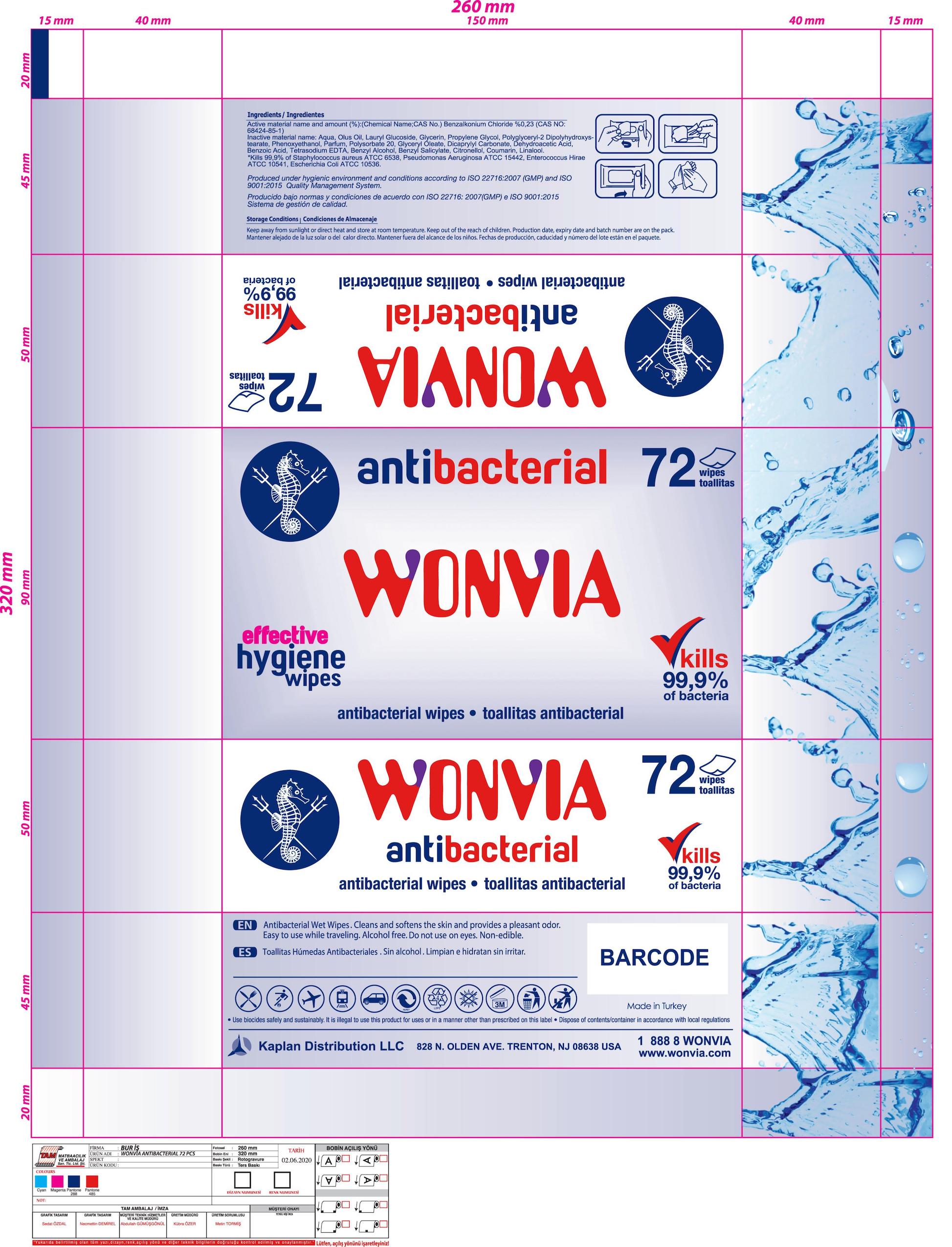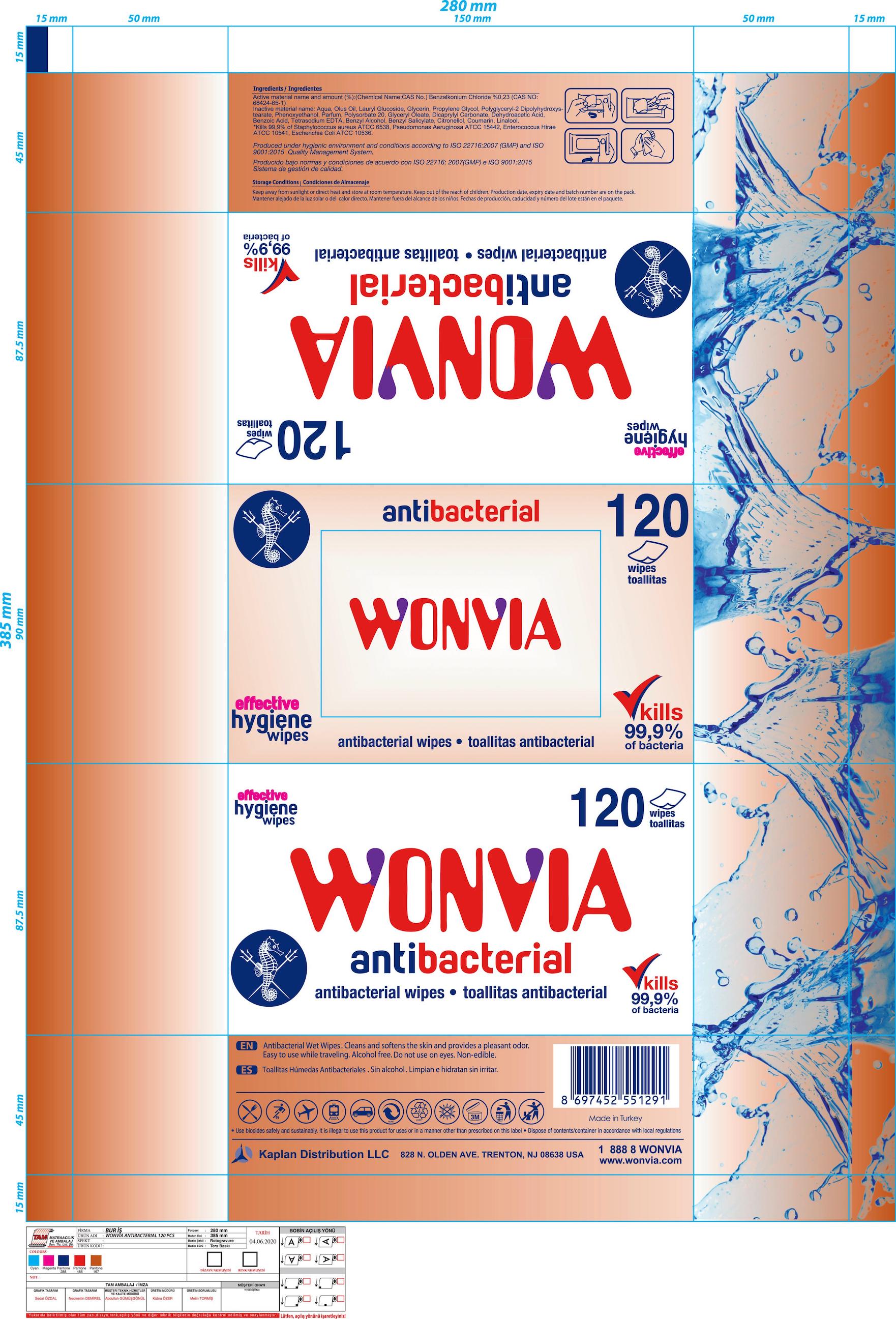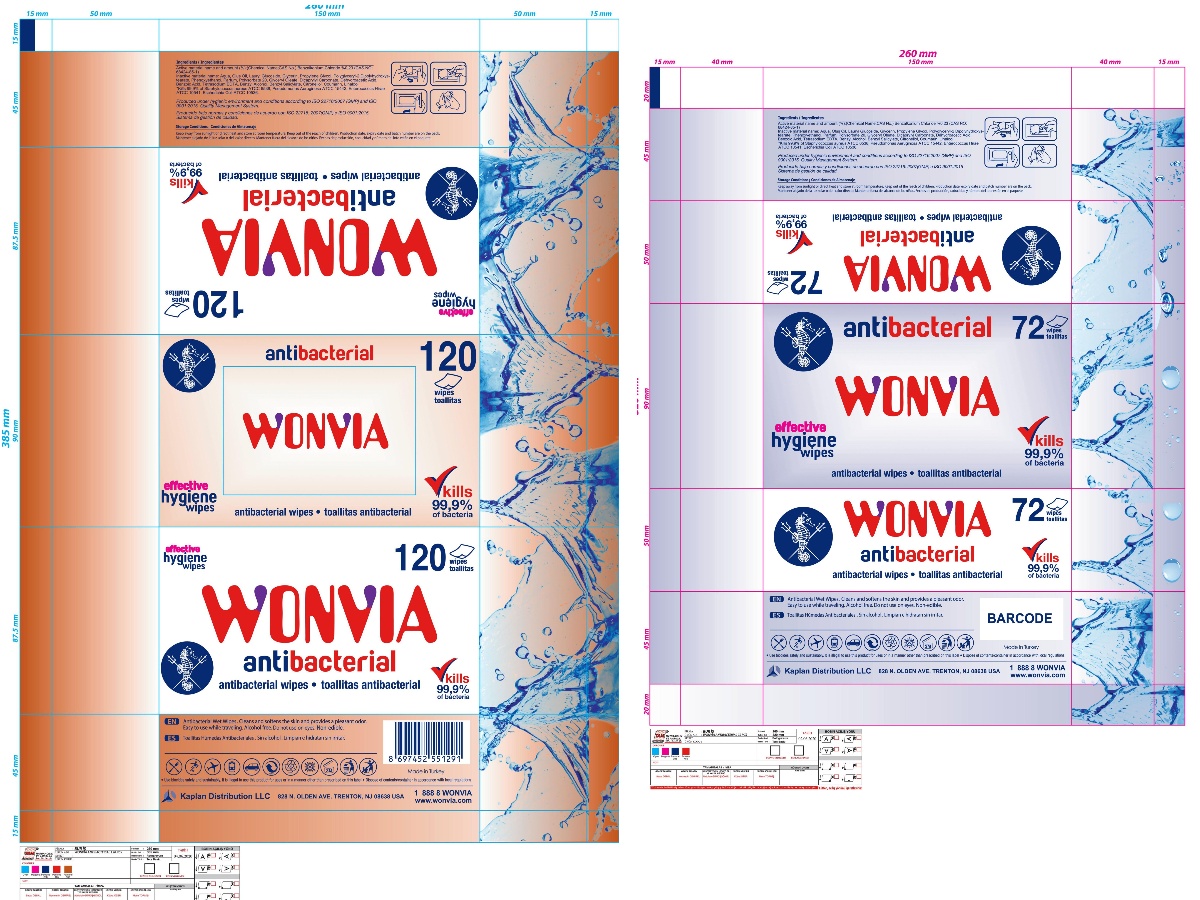 DRUG LABEL: Wonvia Antibacterial Wipes
NDC: 78876-707 | Form: CLOTH
Manufacturer: Kaplan Distribution LLC
Category: otc | Type: HUMAN OTC DRUG LABEL
Date: 20200812

ACTIVE INGREDIENTS: BENZALKONIUM CHLORIDE 0.23 g/100 g
INACTIVE INGREDIENTS: POLYSORBATE 20; BENZOIC ACID; PROPYLENE GLYCOL; BENZYL ALCOHOL; COUMARIN; LINALOOL, (+)-; DICAPRYLYL CARBONATE; EDETATE SODIUM; BENZYL SALICYLATE; GLYCERIN; WATER; .BETA.-CITRONELLOL, (R)-; LAURYL GLUCOSIDE; POLYGLYCERYL-2 DIPOLYHYDROXYSTEARATE; PHENOXYETHANOL; GLYCERYL OLEATE; DEHYDROACETIC ACID

DESCRIPTION

Wonvia antibacterial wipes

Active Ingredient(s)

Active material name and amount (%): (Chemical Name; CAS No.) Benzalkonium Chloride %0,23 (CAS NO: 68424-85-1)

Inactive ingredients

Inactive material name: Aqua, Olus Oil, Lauryl Glucoside, Glycerin, Propylene Glycol, Polyglyceryl-2 Dipolyhydroxystearate, Phenoxyethanol, Parfum, Polysorbate 20, Glyceryl Oleate, Dicaprylyl Carbonate, Dehdroacetic Acid, Benzoic Acid, Tetrasodium EDTA, Benzyl Alcohol, Benzyl Salicylate, Citronellol, Coumarin, Linalool.

Purpose

Antibacterial Wet Wipes.

DOSAGE AND ADMINISTRATION

It is illegal to use this product for uses or in a manner other than prescribed on this label

Use

Antibacterial Wet Wipes. Cleans and softens the skin and provides a pleasant odor.

Warnings

Non-edible.

Do not use on eyes.

STORAGE AND HANDLING

Keep away from sunlight or direct heat and store at room temperature.

Keep out of the reach of children.

DISPOSAL AND WASTE HANDLING

Dispose of contents/container in accordance with local regulations.

QUESTIONS

1 888 8 WONVIA

www.wonvia.com

Package Label - Principal Display Panel

WONVIA antibacterial

antibacterial wipes

kills 99,9% of bacteria

120 wipes

effective hygiene wipes

Use biocides safely and sustainably.

Production date, expiry date and batch number are on the pack.

Kaplan Distribution LLC

828 N. OLDEN AVE. TRENTON, NJ 08638 USA

Made in Turkey

Produced under hygienic environment and conditions according to ISO 22716:2007 (GMP) and ISO 9001:2015 Quality Management System.